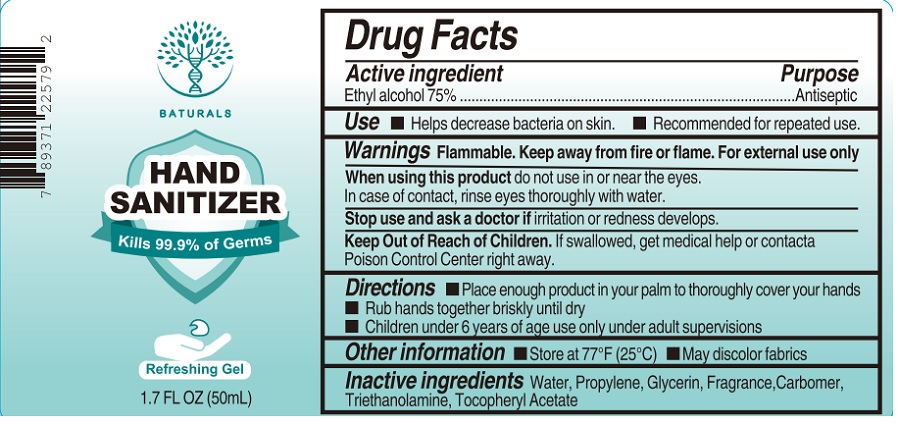 DRUG LABEL: BATURALS HAND SANITIZER
NDC: 74218-001 | Form: GEL
Manufacturer: Guangdong Authenmole Biotech Inc.
Category: otc | Type: HUMAN OTC DRUG LABEL
Date: 20200407

ACTIVE INGREDIENTS: ALCOHOL 75 mL/100 mL
INACTIVE INGREDIENTS: WATER; PROPYLENE; GLYCERIN; CARBOMER HOMOPOLYMER, UNSPECIFIED TYPE; TROLAMINE; .ALPHA.-TOCOPHEROL ACETATE

BATURALS HAND SANITIZER

Active ingredient

Ethyl alcohol 75%

Purpose

Antiseptic

INDICATIONS AND USAGE

Use ▪ Helps decrease bacteria on skin. ▪ Recommended for repeated use.

WARNINGS

Warnings Flammable. Keep away from fire or flame. For external use only

When using this product do not use in or near the eyes.

In case of contact, rinse eyes thoroughly with water.

Stop use and ask a doctor if irritation or redness develops.

Keep Out of Reach of Children. If swallowed, get medical help or contact a Poison Control Center right away.

DOSAGE AND ADMINISTRATION

Directions ▪ Place enough product in your palm to thoroughly cover your hands

▪ Rub hands together briskly until dry

▪ Children under 6 years of age use only under adult supervisions

Other information ▪ Store at 77°F (25°C) ▪ May discolor fabrics

Inactive ingredients

Water, Propylene, Glycerin, Fragrance, Carbomer, Triethanolamine, Tocopheryl Acetate

Kills 99.9% of Germs

Refreshing Gel